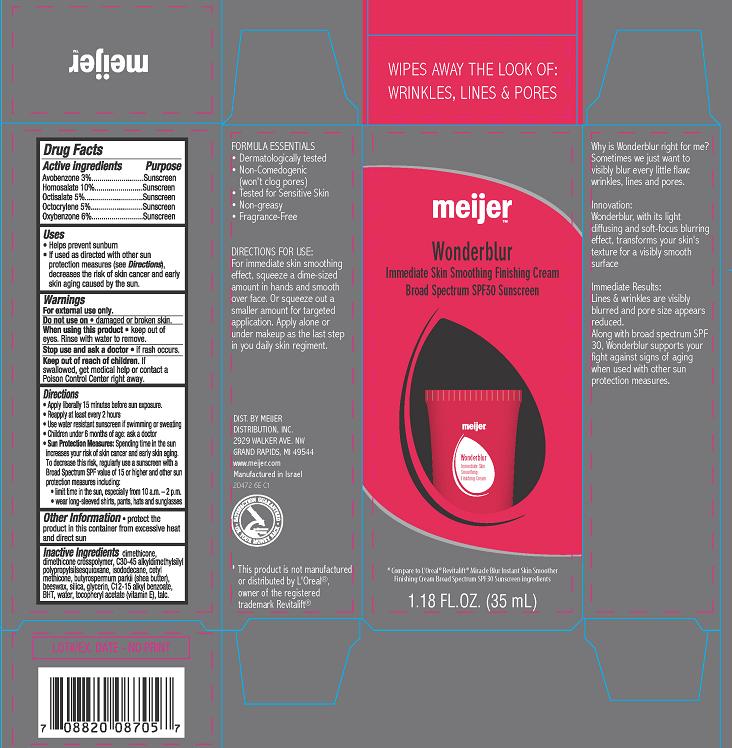 DRUG LABEL: Wonderblur Immediate Skin Smoothing Finishing Broad Spectrum SPF30
NDC: 41250-472 | Form: CREAM
Manufacturer: Meijer Distribution Inc
Category: otc | Type: HUMAN OTC DRUG LABEL
Date: 20131022

ACTIVE INGREDIENTS: AVOBENZONE 3 g/100 mL; HOMOSALATE 10 g/100 mL; OCTISALATE 5 g/100 mL; OCTOCRYLENE 5 g/100 mL; OXYBENZONE 6 g/100 mL
INACTIVE INGREDIENTS: DIMETHICONE; DIMETHICONE/DIENE DIMETHICONE CROSSPOLYMER; ISODODECANE; CETYL DIMETHICONE 150; SHEA BUTTER; YELLOW WAX; SILICON DIOXIDE; GLYCERIN; ALKYL (C12-15) BENZOATE; BUTYLATED HYDROXYTOLUENE; WATER; .ALPHA.-TOCOPHEROL ACETATE; TALC; C30-45 ALKYL METHICONE

meijerTM Wonderblur Immediate Skin Smoothing Finishing Cream
Broad Spectrum SPF30 Sunscreen

Active ingredient

Avobenzone 3.0%
Homosalate 10.0%
Octisalate 5.0%
Octocrylene 5.0%
Oxybenzone 6.0%

Purpose

Sunscreen

Uses

- helps prevent sunburn
- If used as directed with other sun protection measures (see Directions), decreases the risk of skin cancer and early skin aging caused by the sun

Warnings

For external use only.

Do not use on

- damaged or broken skin.

When using this product

- keep out of eyes. Rinse with water to remove.

Stop use and ask a doctor

- if rash occurs.

Keep Out of Reach of Children.

If swallowed, get medical help or contact a Poison Control Center right away.

Directions

- Apply liberally 15 minutes before sun exposure.
- Reapply at least every 2 hours
- Use water resistant sunscreen if swimming or sweating
- Children under 6 months of age: ask a doctor
- Sun Protection Measures: Spending time in the sun increases your risk of skin cancer and early skin aging. To decrease this risk, regularly use a sunscreen with a Broad Spectrum SPF value of 15 or higher and other sun protection measures including:
  - limit time in the sun, especially from 10 a.m. - 2 p.m.
  - wear long-sleeved shirts, pants, hats and sunglasses

Other Information

- protect the product in this container from excessive heat and direct sun

Inactive ingredients

dimethicone, dimethicone crosspolymer, C30-45 alkyldimethylsilyl polypropylsilsesquioxane, isododecane, cetyl methicone, butyrospermum parkii (shea butter), beeswax, silica, glycerin, C12-15 alkyl benzoate, BHT, water, tocopheryl acetate (vitamin E), talc.

Package/Label Principal Display Panel

meijerTM Wonderblur Immediate Skin Smoothing Finishing Cream
Broad Spectrum SPF30 Sunscreen

*Compare to L'Oreal® Revitalift® Miracle Blur Instant Skin Smoother
Finishing Cream Broad Spectrum SPF30 Sunscreen ingredients

1.18 FL OZ (35 mL)

DIST BY MEIJER
DISTRIBUTION, INC.
2929 WALKER AVE, NW
GRAND RAPIDS, MI 49544

www.meijer.com

Manufactured in Israel

2D472 6E C1

*This product is not manufactured or distributed by L'Oreal®, owner of the registered trademark Revitalift®.

Label